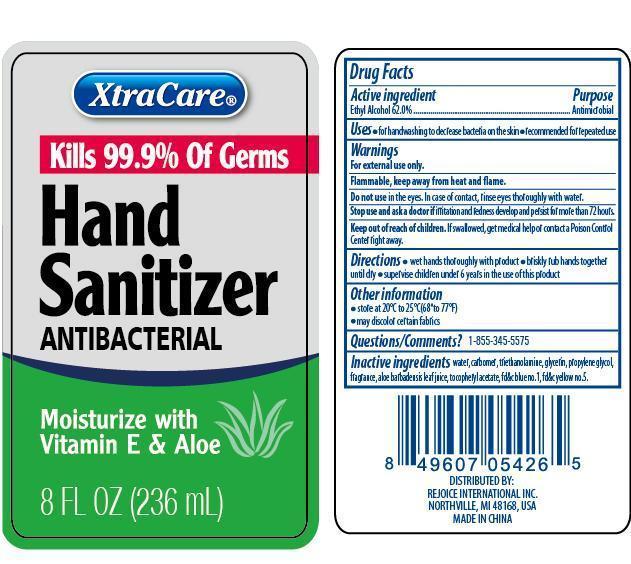 DRUG LABEL: XtraCare Hand Sanitizer
NDC: 57337-044 | Form: GEL
Manufacturer: Rejoice International
Category: otc | Type: HUMAN OTC DRUG LABEL
Date: 20240228

ACTIVE INGREDIENTS: ALCOHOL 146 g/236 g
INACTIVE INGREDIENTS: WATER; CARBOMER COPOLYMER TYPE A (ALLYL PENTAERYTHRITOL CROSSLINKED); TROLAMINE; GLYCERIN; PROPYLENE GLYCOL; ALOE VERA LEAF; .ALPHA.-TOCOPHEROL ACETATE; FD&C BLUE NO. 1; FD&C YELLOW NO. 5

XtraCare Hand Sanitizer

Active Ingredients Purpose

Ethyl Alcohol 62.0% ................................ Antimicrobial

Uses

- for handwashing to decrease bacteria on the skin
- recommended for repeated use

Keep out of reach of children. If swallowed, get medical help or contact a Poison Control Center right away.

INDICATIONS AND USAGE

XtraCare® Hand Sanitizer Antibacterial

Kills 99.9% of Germs

Moisturize with Vitamin E & Aloe

8 Fl Oz (236 mL)

Warnings

For external use only.

Flammable, keep away from heat and flame.

Do not use in the eyes. In case of contact, rinse eyes thoroughly with water.

Stop use and ask a doctor if irritation and redness develop and persist for more than 72 hours.

Directions

- wet hands thoroughly with product
- briskly rub hands together until dry
- supervise children under 6 years in the use of this product

Inactive Ingredients

water, carbomer, triethanolamine, glycerin, propylene glycol, fragrance, aloe barbadensis leaf juice, tocopheryl acetate, fd&c blue no. 1, fd&c yellow no.5

Other information

- store at 20oC to 25oC (68o to 77oF)
- may discolor certain fabrics

Questions/Comments? 1-855-345-5575

DISTRIBUTED BY:

REJOICE INTERNATIONAL, INC

NORTHVILLE, MI 48168. USA

MADE IN CHINA